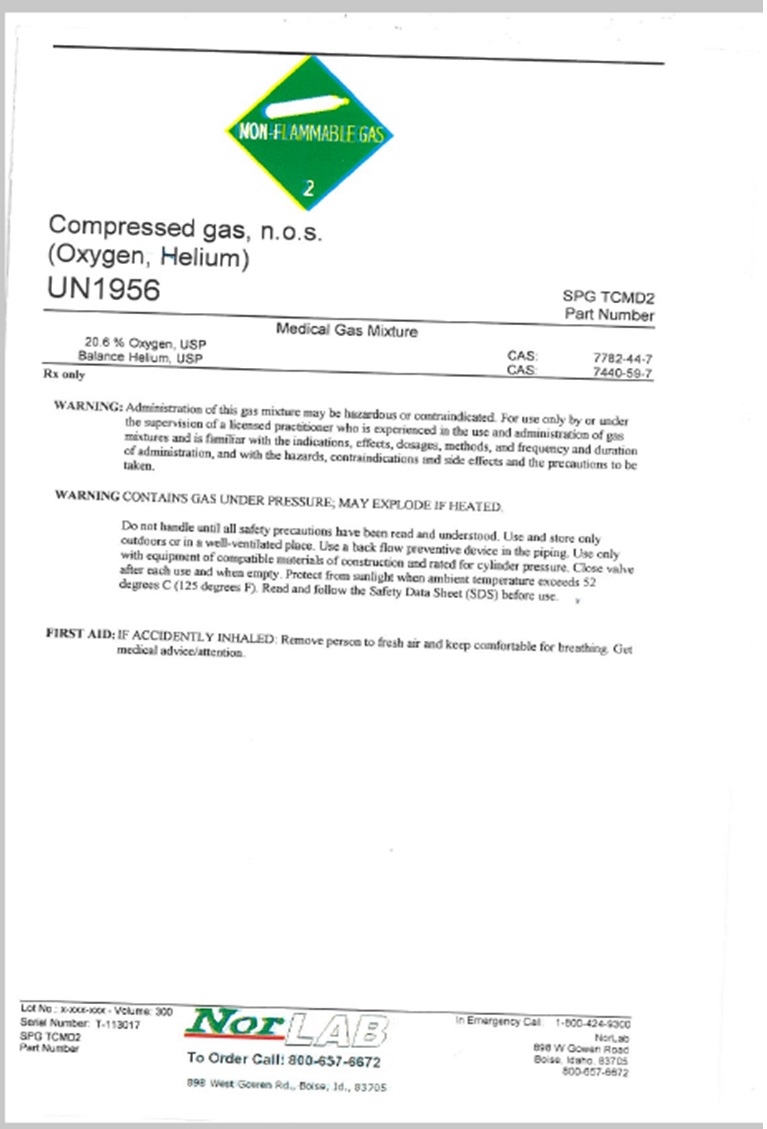 DRUG LABEL: COMPRESSED Gas, N.O.S.
NDC: 42602-007 | Form: GAS
Manufacturer: Norco, Inc.
Category: prescription | Type: HUMAN PRESCRIPTION DRUG LABEL
Date: 20251215

ACTIVE INGREDIENTS: OXYGEN 20.4 L/100 L; HELIUM 79.6 L/100 L

COMPRESSED GAS, N.O.S. LABEL 20.6% OXYGEN BALANCE HELIUM, USP

Compressed gas, n.o.s.
(Oxygen, Helium)
UN1956 SPG TCMD2

Part Number

___________________________________________________________________________

Medical Gas Mixture
20.6% Oxygen, USP CAS: 7782-44-7
Balance Heliun, USP CAS: 7440-59-7

___________________________________________________________________________

Rx only

WARNING: Administration of this gas mixture may be hazardous or contraindicated. For use only by or under
the supervision of a licensed practitioner who is experienced in the use and administration of gas
mixtures and is familiar with the indications, effects, dosages, methods, and frequency and duration
of administration, and with the hazards, contraindications and side effects and the precautions to be
taken.

WARNING: CONTAINS GAS UNDER PRESSURE; MAY EXPLODE IF HEATED.

Do not handle until all safety precautions have been read and understood. Use and store only

outdoors or in a well-ventilated place. Use a back flow preventive device in the piping. Use only
with equipment of compatible materials of construction and rated for cylinder pressure. Close valve after
after each use and when empty. Protect from sunlight when ambient temperature exceeds 52
degrees C (125 degrees F). Read and follow the Safety Data Sheet (SDS) before use.

FIRST AID: IF ACCIDENTALLY INHALED; Remove to fresh air and keep comfortable for breathing. Get
medical advice/attention.

___________________________________________________________________________________________________
Lot No: x-xxx-xxx – Volume 300 NorLAB In Emergency Call: 1-800-424-9300
Serial Number: T-113017 To Order Call: 800-657-6672 NorLab
SPG TCMD2 898 W. Gowen Road

Part Number Boise, ID 83507

800-657-6572

res